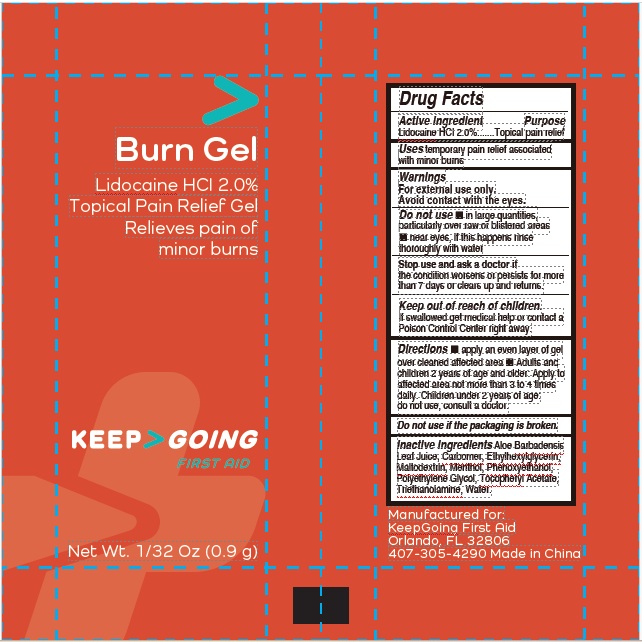 DRUG LABEL: Burn
NDC: 82942-1001 | Form: GEL
Manufacturer: J&A Digital Inc.
Category: otc | Type: HUMAN OTC DRUG LABEL
Date: 20250602

ACTIVE INGREDIENTS: LIDOCAINE HYDROCHLORIDE 20 mg/1 g
INACTIVE INGREDIENTS: ALOE VERA LEAF; CARBOMER HOMOPOLYMER, UNSPECIFIED TYPE; ETHYLHEXYLGLYCERIN; MALTODEXTRIN; MENTHOL; POLYETHYLENE GLYCOL, UNSPECIFIED; PHENOXYETHANOL; TROLAMINE; .ALPHA.-TOCOPHEROL ACETATE; WATER

Burn

Active ingredient

Lidocaine HCl 2.0%

Purpose

Topical pain relief

Uses

temporary pain relief associated with minor burns

Warnings

For external use only

Do not use

- in large quantities, particularly over raw or blistered areas
- near eyes, if this happens rinse thoroughly with water

Stop use

and ask a doctor if the condition worsens or persists for more than 7 days or clears up and returns.

Keep out of reach of children.

If swallowed get medical help or contact a Poison Control Center right away.

Directions

- apply an even layer of gel over cleaned affected area
- not to be used on children under 12 years

Inactive ingredients

Aloe Barbadensis Leaf Juice, Carbomer, Ethylhexylglycerin, Maltodextrin, Menthol, Polyethylene Glycol, Phenoxyethanol, Triethanolamine, Tocopheryl Acetate, Water.